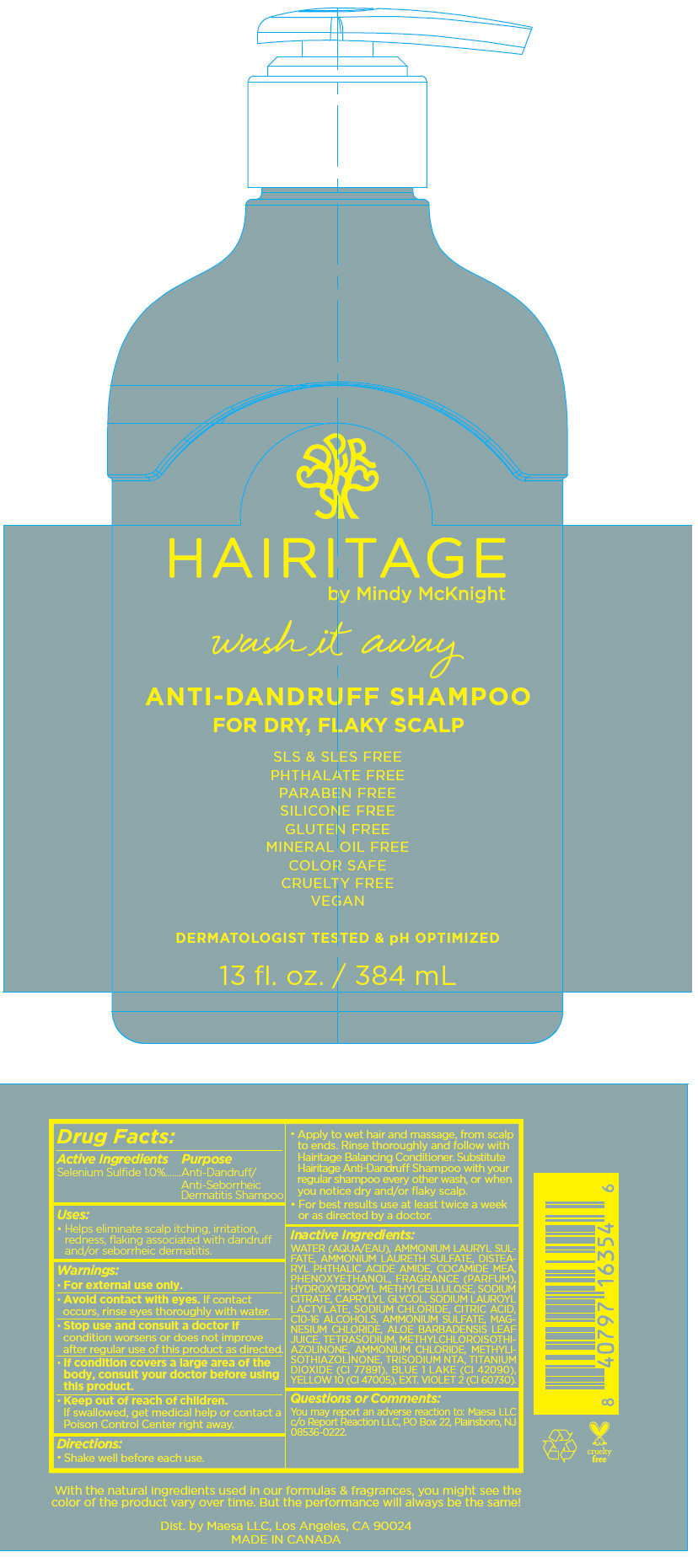 DRUG LABEL: Hairitage Wash It Away Anti-Dandruff for Dry, Flaky Scalp
NDC: 71899-068 | Form: LIQUID
Manufacturer: Maesa, LLC.
Category: otc | Type: HUMAN OTC DRUG LABEL
Date: 20241112

ACTIVE INGREDIENTS: Selenium Sulfide 0.1 g/1 mL
INACTIVE INGREDIENTS: Water; ALOE VERA LEAF; AMMONIUM LAURETH-12 SULFATE; Phenoxyethanol; Caprylyl Glycol; Ammonium Lauryl Sulfate; Ammonium Sulfate; Ammonium Chloride; EDETATE SODIUM; Trisodium Nitrilotriacetate; Methylchloroisothiazolinone; Methylisothiazolinone; DISTEARYL PHTHALAMIC ACID; COCO MONOETHANOLAMIDE; Titanium Dioxide; HYPROMELLOSE, UNSPECIFIED; Sodium Chloride; CITRIC ACID MONOHYDRATE; Sodium Lauroyl Lactylate; SODIUM CITRATE, UNSPECIFIED FORM; Magnesium Chloride; Magnesium Nitrate; FD&C BLUE NO. 1; D&C YELLOW NO. 10; EXT. D&C VIOLET NO. 2

Hairitage Wash It Away Anti-Dandruff Shampoo for Dry, Flaky Scalp

Drug Facts:

Active Ingredients

Selenium Sulfide 1.0%

Purpose

Anti-Dandruff/Anti-Seborrheic Dermatitis Shampoo

Uses

- Helps eliminate scalp itching, irritation, redness, flaking associated with dandruff and/or seborrheic dermatitis.

Warnings

- For external use only.
- Avoid contact with eyes. If contact occurs, rinse eyes thoroughly with water.
- Stop use and consult a doctor if condition worsens or does not improve after regular use of this product as directed.
- If condition covers a large area of the body, consult your doctor before using this product.

- Keep out of reach of children.
  If swallowed, get medical help or contact a Poison Control Center right away.

Directions

- Shake well before each use.
- Apply to wet hair and massage, from scalp to ends. Rinse thoroughly and follow with Hairitage Balancing Conditioner. Substitute Hairitage Anti-Dandruff Shampoo with your regular shampoo every other wash, or when you notice dry and/or flaky scalp.
- For best results use at least twice a week or as directed by a doctor.

Inactive Ingredients

WATER (AQUA/EAU), AMMONIUM LAURYL SULFATE, AMMONIUM LAURETH SULFATE, DISTEARYL PHTHALIC ACIDE AMIDE, COCAMIDE MEA, PHENOXYETHANOL, FRAGRANCE (PARFUM), HYDROXYPROPYL METHYLCELLULOSE, SODIUM CITRATE, CAPRYLYL GLYCOL, SODIUM LAUROYL LACTYLATE, SODIUM CHLORIDE, CITRIC ACID, C10-16 ALCOHOLS, AMMONIUM SULFATE, MAGNESIUM CHLORIDE, ALOE BARBADENSIS LEAF JUICE, TETRASODIUM, METHYLCHLOROISOTHIAZOLINONE, AMMONIUM CHLORIDE, METHYLISOTHIAZOLINONE, TRISODIUM NTA, TITANIUM DIOXIDE (CI 77891), BLUE 1 LAKE (CI 42090), YELLOW 10 (CI 47005), EXT. VIOLET 2 (CI 60730).

Questions or Comments

You may report an adverse reaction to: Maesa LLC c/o Report Reaction LLC, PO Box 22, Plainsboro, NJ 08536-0222.

Dist. by Maesa LLC, Los Angeles, CA 90024

PRINCIPAL DISPLAY PANEL - 384 mL Bottle Label

HAIRITAGE
by Mindy McKnight

wash it away

ANTI-DANDRUFF SHAMPOO
FOR DRY, FLAKY SCALP

SLS & SLES FREE
PHTHALATE FREE
PARABEN FREE
SILICONE FREE
GLUTEN FREE
MINERAL OIL FREE
COLOR SAFE
CRUELTY FREE
VEGAN

DERMATOLOGIST TESTED & pH OPTIMIZED

13 fl. oz. / 384 mL